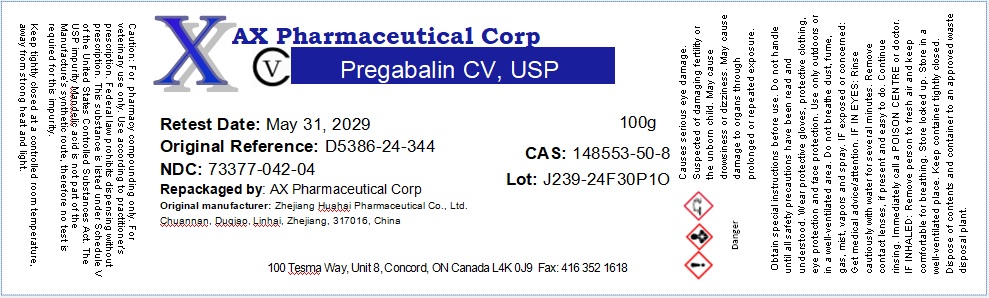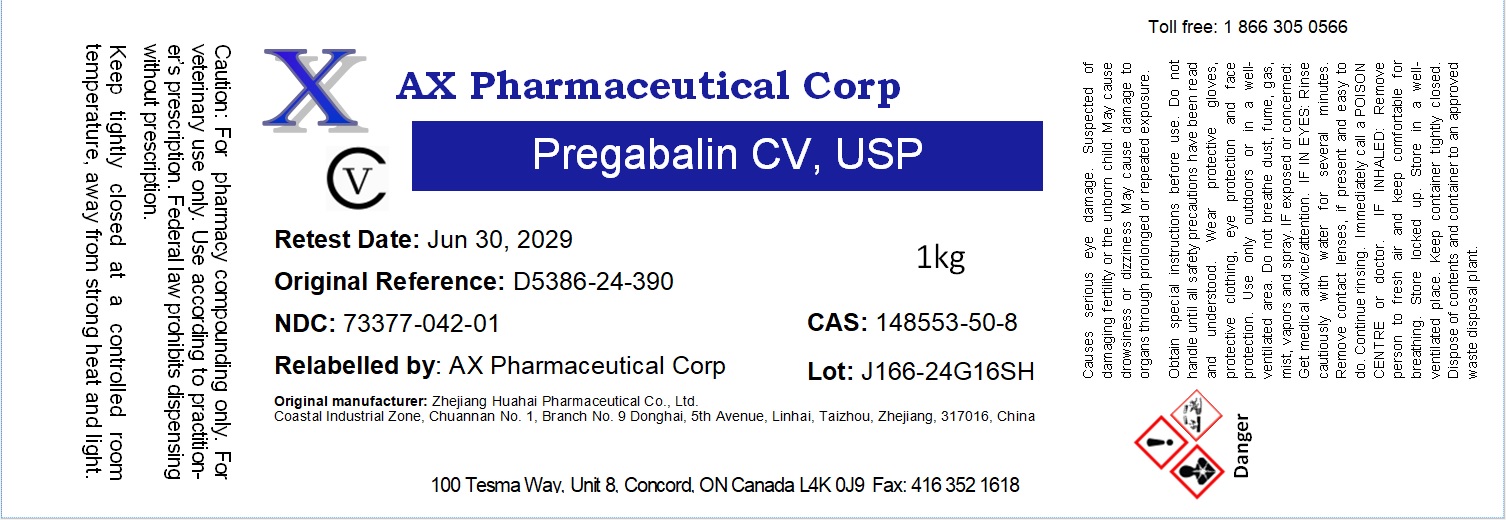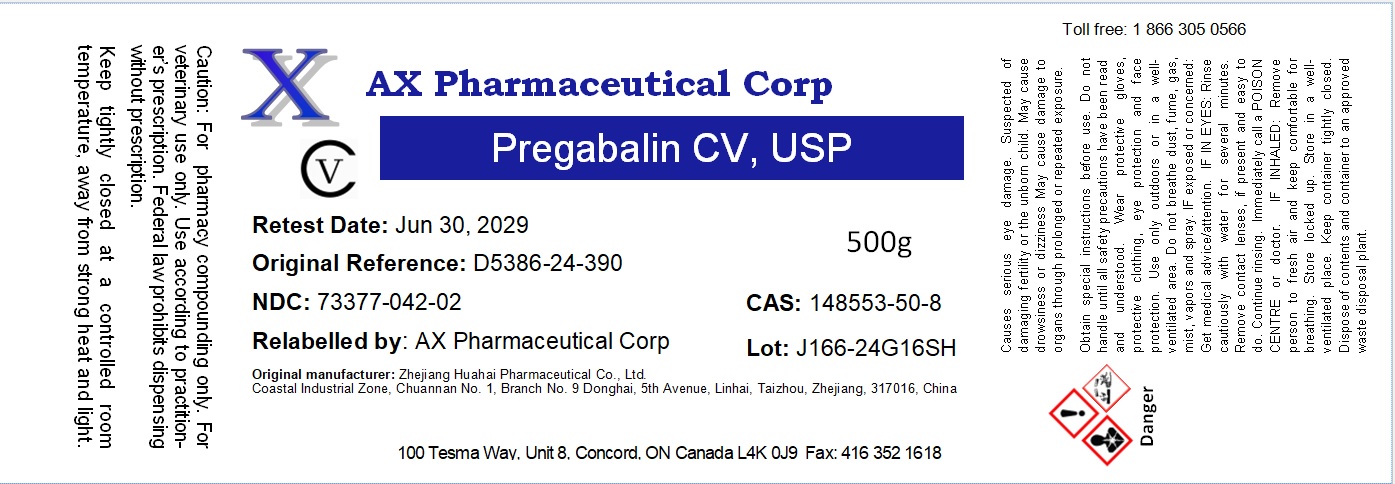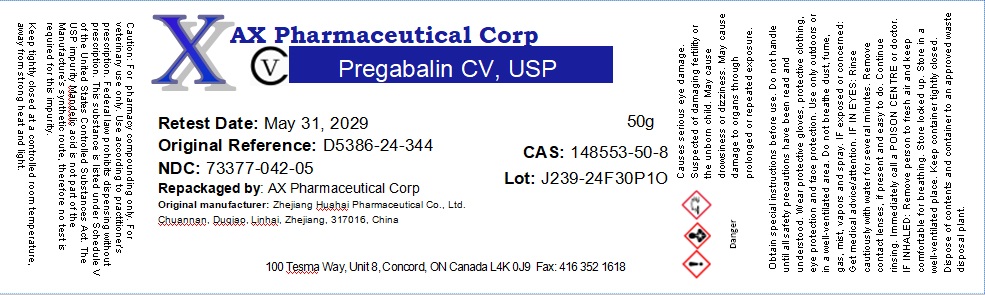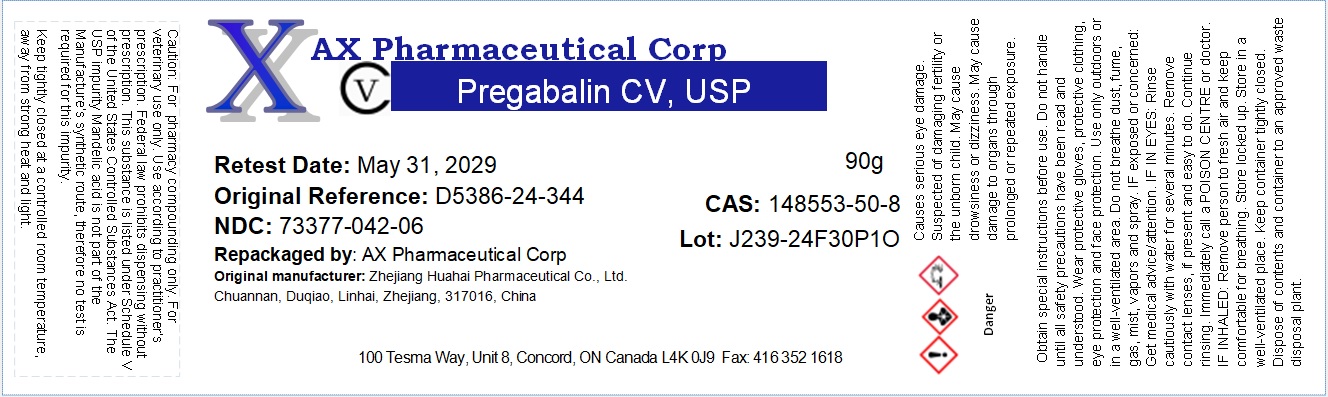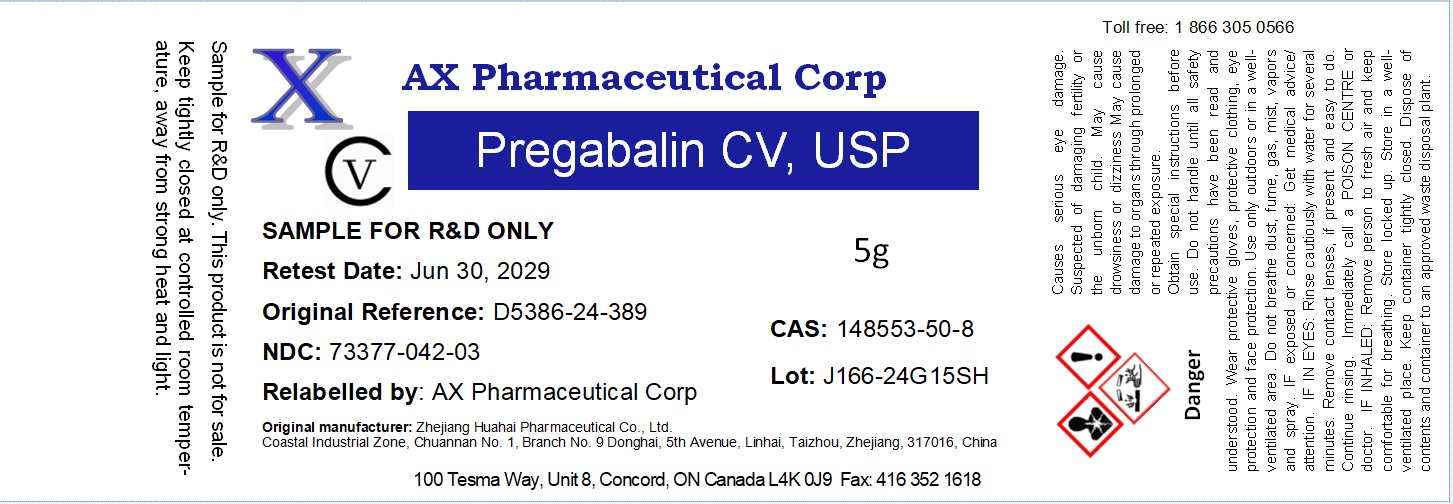 DRUG LABEL: Pregabalin
NDC: 73377-042 | Form: POWDER
Manufacturer: AX Pharmaceutical Corp
Category: other | Type: BULK INGREDIENT - ANIMAL DRUG
Date: 20250210
DEA Schedule: CV

ACTIVE INGREDIENTS: PREGABALIN 1 kg/1 kg

Pregabalin